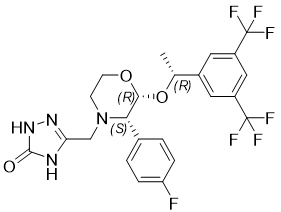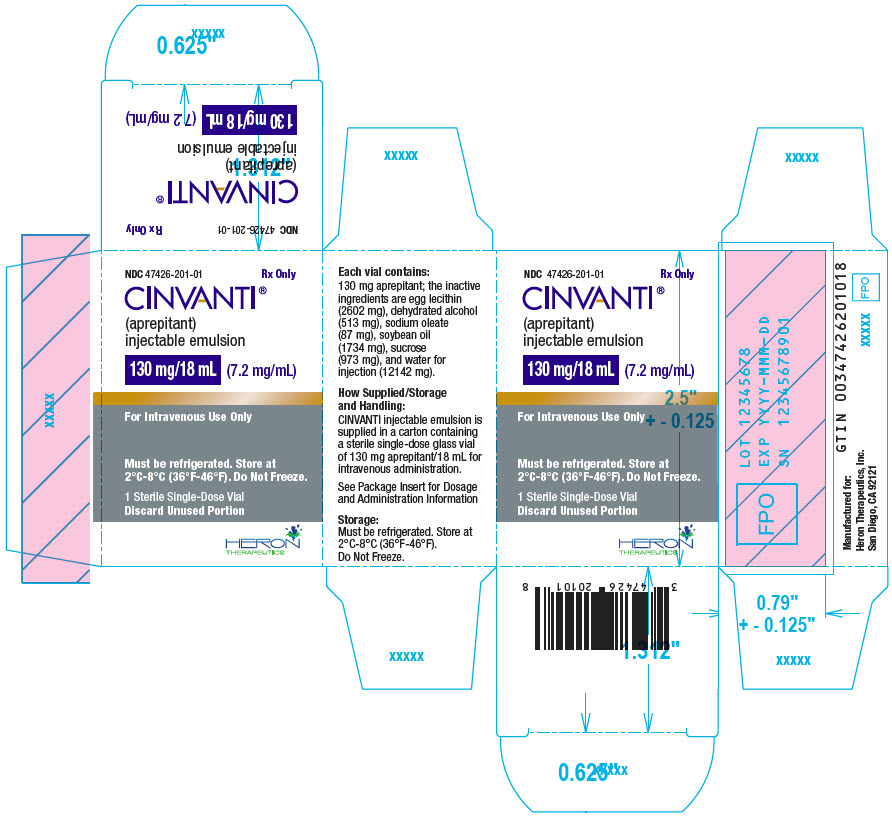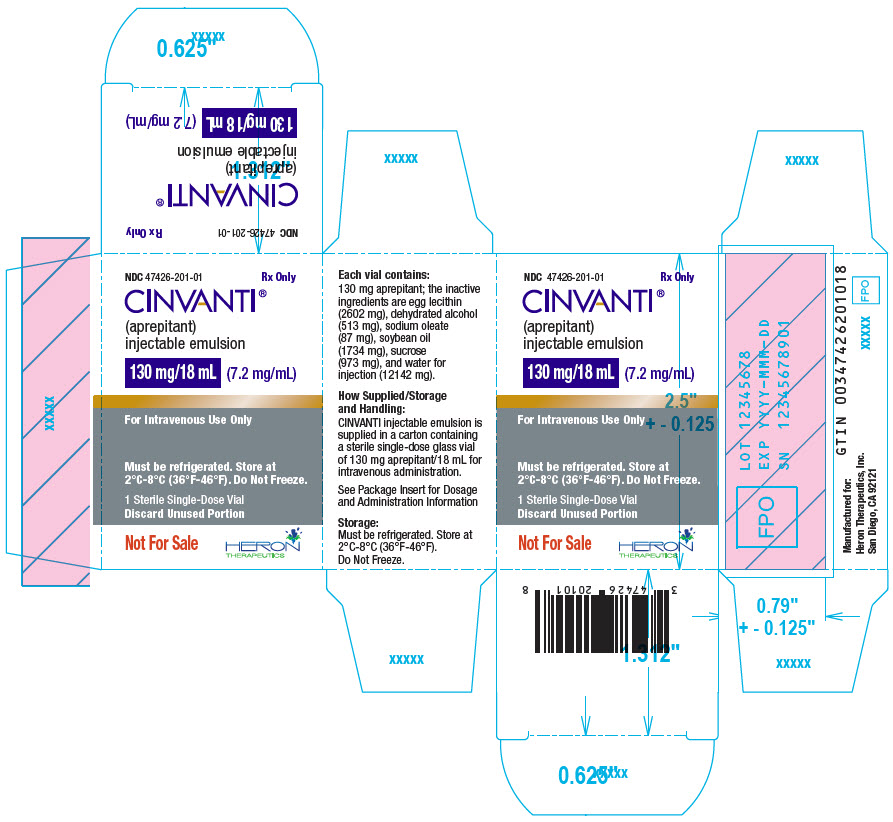 DRUG LABEL: CINVANTI
NDC: 47426-201 | Form: INJECTION, EMULSION
Manufacturer: Heron Therapeutics, Inc.
Category: prescription | Type: HUMAN PRESCRIPTION DRUG LABEL
Date: 20251121

ACTIVE INGREDIENTS: APREPITANT 130 mg/18 mL
INACTIVE INGREDIENTS: EGG PHOSPHOLIPIDS 2602 mg/18 mL; ALCOHOL 513 mg/18 mL; SODIUM OLEATE 87 mg/18 mL; SOYBEAN OIL 1734 mg/18 mL; SUCROSE 973 mg/18 mL; WATER 12142 mg/18 mL

HIGHLIGHTS OF PRESCRIBING INFORMATION

These highlights do not include all the information needed to use CINVANTI® safely and effectively. See full prescribing information for CINVANTI.
CINVANTI® (aprepitant) injectable emulsion, for intravenous use
Initial U.S. Approval: 2003

1 INDICATIONS AND USAGE

CINVANTI is a substance P/neurokinin-1 (NK1) receptor antagonist, indicated in adults, in combination with other antiemetic agents, for the prevention of:

- acute and delayed nausea and vomiting associated with initial and repeat courses of highly emetogenic cancer chemotherapy (HEC) including high-dose cisplatin as a single-dose regimen. (1)
- delayed nausea and vomiting associated with initial and repeat courses of moderately emetogenic cancer chemotherapy (MEC) as a single-dose regimen. (1)
- nausea and vomiting associated with initial and repeat courses of MEC as a 3-day regimen. (1)

Limitations of Use:

CINVANTI has not been studied for treatment of established nausea and vomiting. (1)

2 DOSAGE AND ADMINISTRATION

Recommended Dosage (2.1):

- Administer CINVANTI intravenously as an injection over 2 minutes or an infusion over 30 minutes; complete the injection or infusion approximately 30 minutes prior to chemotherapy.
- HEC and MEC (Single-Dose Regimen): The recommended dosage in adults is 130 mg on Day 1.
- MEC (3-Day Regimen): The recommended dosage in adults is 100 mg on Day 1. Aprepitant capsules (80 mg) are given orally on Days 2 and 3.
- CINVANTI is part of a regimen that includes a corticosteroid and a 5-HT3 antagonist.

Preparation:

- See the full prescribing information for instructions. (2.2)

3 DOSAGE FORMS AND STRENGTHS

Injectable emulsion: 130 mg/18 mL (7.2 mg/mL) aprepitant in single-dose vial (3)

4 CONTRAINDICATIONS

- Known hypersensitivity to any component of this drug. (4, 5.2)
- Concurrent use with pimozide. (4)

5 WARNINGS AND PRECAUTIONS

- CYP3A4 Interactions: Aprepitant is a substrate, weak-to-moderate (dose-dependent) inhibitor and an inducer of CYP3A4; see Full Prescribing Information for recommendations regarding contraindications, risk of adverse reactions, and dosage adjustment of CINVANTI and concomitant drugs. (4, 5.1, 7.1, 7.2)
- Hypersensitivity Reactions (including anaphylaxis): May occur during or soon after administration. If symptoms occur, discontinue CINVANTI and do not reinitiate it. (4, 5.2)
- Warfarin (a CYP2C9 substrate): Risk of decreased INR of prothrombin time; monitor INR in 2–week period, particularly at 7 to 10 days, following initiation of CINVANTI. (5.3, 7.1)
- Hormonal Contraceptives: Efficacy of contraceptives may be reduced during and for 28 days following administration of aprepitant. Use effective alternative or back-up methods of non-hormonal contraception. (5.4, 7.1, 8.3)

6 ADVERSE REACTIONS

Most common adverse reactions are:

- Single-dose fosaprepitant with MEC (≥2%): fatigue, diarrhea, neutropenia, asthenia, anemia, peripheral neuropathy, leukopenia, dyspepsia, urinary tract infection, pain in extremity. (6.1)
- 3-day oral aprepitant with MEC (≥1% and greater than standard therapy): fatigue and eructation. (6.1)
- Single-dose fosaprepitant with HEC: generally similar to 3-day oral aprepitant. In addition, infusion site reactions (3%) occurred. (6.1)
- Single-dose CINVANTI (≥2%): headache and fatigue. (6.1)

To report SUSPECTED ADVERSE REACTIONS, contact Heron Therapeutics, Inc. at 1-844-437-6611 and www.CINVANTI.com or FDA at 1-800-FDA-1088 or www.fda.gov/medwatch

7 DRUG INTERACTIONS

See full prescribing information for a list of clinically significant drug interactions. (4, 5.1, 5.3, 5.4, 7.1, 7.2)

8 USE IN SPECIFIC POPULATIONS

Pregnancy: May cause fetal harm. (8.1)

FULL PRESCRIBING INFORMATION

1 INDICATIONS AND USAGE

CINVANTI, in combination with other antiemetic agents, is indicated in adults for the prevention of:

- acute and delayed nausea and vomiting associated with initial and repeat courses of highly emetogenic cancer chemotherapy (HEC) including high-dose cisplatin as a single-dose regimen.
- delayed nausea and vomiting associated with initial and repeat courses of moderately emetogenic cancer chemotherapy (MEC) as a single-dose regimen.
- nausea and vomiting associated with initial and repeat courses of MEC as a 3-day regimen.

Limitations of Use

- CINVANTI has not been studied for the treatment of established nausea and vomiting.

2 DOSAGE AND ADMINISTRATION

2.1 Prevention of Nausea and Vomiting Associated with HEC and MEC

The recommended dosages in adults of CINVANTI, dexamethasone, and a 5-HT3 antagonist for the prevention of nausea and vomiting associated with administration of HEC or MEC are shown in Table 1, Table 2 and Table 3 respectively. Administer CINVANTI intravenously either by injection over a two (2) minute period or by infusion over a thirty (30) minute period on Day 1, completing the injection or infusion approximately 30 minutes prior to chemotherapy.

Table 1. Recommended Dosage of CINVANTI for the Prevention of Nausea and Vomiting Associated with HEC (Single-Dose Regimen)
Agent | Day 1 | Day 2 | Day 3 | Day 4
CINVANTI | 130 mg intravenously | None | None | None
Dexamethasone [Administer dexamethasone 30 minutes prior to chemotherapy treatment on Day 1 and in the morning on Days 2 through 4. Also administer dexamethasone in the evenings on Days 3 and 4. A 50% dosage reduction of dexamethasone on Days 1 and 2 is recommended to account for a drug interaction with aprepitant [see Clinical Pharmacology (12.3)].] | 12 mg orally | 8 mg orally | 8 mg orally twice daily | 8 mg orally twice daily
5-HT3 antagonist | See selected 5-HT3 antagonist prescribing information for recommended dosage | None | None | None

Table 2. Recommended Dosage of CINVANTI for the Prevention of Nausea and Vomiting Associated with MEC (Single-Dose Regimen)
Agent | Day 1
CINVANTI | 130 mg intravenously
Dexamethasone [Administer dexamethasone 30 minutes prior to chemotherapy treatment on Day 1. A 50% dosage reduction of dexamethasone is recommended to account for a drug interaction with aprepitant [see Clinical Pharmacology (12.3)].] | 12 mg orally
5-HT3 antagonist | See selected 5-HT3 antagonist prescribing information for recommended dosage

Table 3. Recommended Dosage of CINVANTI for the Prevention of Nausea and Vomiting Associated with MEC (3-Day Regimen with Oral Aprepitant on Days 2 and 3)
Agent | Day 1 | Day 2 | Day 3
CINVANTI | 100 mg intravenously | None | None
Oral Aprepitant | None | 80 mg orally | 80 mg orally
Dexamethasone [Administer dexamethasone 30 minutes prior to chemotherapy treatment on Day 1. A 50% dosage reduction of dexamethasone is recommended to account for a drug interaction with aprepitant [see Clinical Pharmacology (12.3)].] | 12 mg orally | None | None
5-HT3 antagonist | See selected 5-HT3 antagonist prescribing information for recommended dosage | None | None

2.2 Preparation of CINVANTI for Administration

Intravenous Injection over a period of 2 minutes

For intravenous injection over a period of 2 minutes, administer 130 mg of CINVANTI as part of a HEC or MEC regimen or 100 mg as part of a MEC regimen as a single dose on Day 1.

Aseptically withdraw 18 mL for the 130 mg dose or 14 mL for the 100 mg dose from the vial. Do not dilute.

The infusion line should be flushed with normal saline before and after administration of CINVANTI.

Intravenous Infusion over a period of 30 minutes

Table 4 includes preparation instructions for CINVANTI for HEC or MEC as a 130 mg single-dose regimen, and for MEC as a 100 mg single-dose followed by 2 days of oral aprepitant as a 3-day regimen. Differences in preparation for each dose are displayed as bolded text.

Table 4. Preparation Instructions for CINVANTI Intravenous Infusion
Step 1 | Aseptically withdraw 18 mL for the 130 mg dose or 14 mL for the 100 mg dose from the vial and transfer it into an infusion bag [Use only Non-DEHP tubing, non-PVC infusion bags] filled with 100 mL of 0.9% Sodium Chloride Injection, USP or 5% Dextrose for Injection, USP.
Step 2 | Gently invert the bag 4 to 5 times. Avoid shaking.
Step 3 | Before administration, inspect the bag for particulate matter and discoloration. Discard the bag if particulate and/or discoloration are observed.
Note: The differences in preparation for each recommended dosage of CINVANTI are displayed in bolded text (see Table 1 for HEC Regimen and Table 2 for MEC Regimen).

Caution: Do not mix CINVANTI with solutions for which physical and chemical compatibility have not been established.

In-Use Storage Conditions for CINVANTI in Acceptable Intravenous Diluents

Diluted CINVANTI solution is stable at ambient room temperature for up to 6 hours in 0.9% Sodium Chloride Injection, USP or 12 hours in 5% Dextrose Injection, USP or up to 72 hours if stored under refrigeration in 0.9% Sodium Chloride Injection, USP or in 5% Dextrose Injection, USP.

2.3 Compatibilities

CINVANTI is compatible with 0.9% Sodium Chloride Injection, USP or 5% Dextrose Injection, USP.

2.4 Incompatibilities

CINVANTI is incompatible with any solutions containing divalent cations (e.g. calcium, magnesium), including Lactated Ringer's Solution and Hartmann's Solution.

3 DOSAGE FORMS AND STRENGTHS

Injectable emulsion: 130 mg/18 mL (7.2 mg/mL) aprepitant as an opaque, off-white to amber emulsion, in single-dose vial

4 CONTRAINDICATIONS

CINVANTI is contraindicated in patients:

- who are hypersensitive to any component of the product [see Description (11)]. Hypersensitivity reactions including anaphylaxis have been reported [see Warnings and Precautions (5.2), Adverse Reactions (6.2)].
- taking pimozide. Inhibition of CYP3A4 by aprepitant could result in elevated plasma concentrations of pimozide, which is a CYP3A4 substrate, potentially causing serious or life-threatening reactions, such as QT prolongation, a known adverse reaction of pimozide [see Warnings and Precautions (5.1)].

5 WARNINGS AND PRECAUTIONS

5.1 Clinically Significant CYP3A4 Drug Interactions

Aprepitant is a substrate, weak-to-moderate (dose-dependent) inhibitor, and an inducer of CYP3A4.

- Use of CINVANTI with other drugs that are CYP3A4 substrates may result in increased plasma concentration of the concomitant drug.
  - Use of pimozide with CINVANTI is contraindicated due to the risk of significantly increased plasma concentrations of pimozide, potentially resulting in prolongation of the QT interval, a known adverse reaction of pimozide [see Contraindications (4)].
- Use of CINVANTI with strong or moderate CYP3A4 inhibitors (e.g., ketoconazole, diltiazem) may increase plasma concentrations of aprepitant and result in an increased risk of adverse reactions related to CINVANTI.
- Use of CINVANTI with strong CYP3A4 inducers (e.g., rifampin) may result in a reduction in aprepitant plasma concentrations and decreased efficacy of CINVANTI.

See Table 8 and Table 9 for a listing of potentially significant drug interactions [see Drug Interactions (7.1, 7.2)].

5.2 Hypersensitivity Reactions

Serious hypersensitivity reactions, including anaphylaxis during or soon after administration of CINVANTI have occurred. Symptoms including dyspnea, eye swelling, flushing, pruritus and wheezing have been reported [see Adverse Reactions (6.2)].

Monitor patients during and after administration. If hypersensitivity reactions occur, discontinue CINVANTI and administer appropriate medical therapy. Do not reinitiate CINVANTI in patients who experience these symptoms with previous use.

5.3 Decrease in INR with Concomitant Warfarin

Coadministration of CINVANTI with warfarin, a CYP2C9 substrate, may result in a clinically significant decrease in the International Normalized Ratio (INR) of prothrombin time [see Clinical Pharmacology (12.3)]. Monitor the INR in patients on chronic warfarin therapy in the 2-week period, particularly at 7 to 10 days, following initiation of CINVANTI with each chemotherapy cycle [see Drug Interactions (7.1)].

5.4 Risk of Reduced Efficacy of Hormonal Contraceptives

Upon coadministration with CINVANTI, the efficacy of hormonal contraceptives may be reduced during administration of and for 28 days following the last dose of CINVANTI [see Clinical Pharmacology (12.3)]. Advise patients to use effective alternative or back-up methods of non-hormonal contraception during treatment with CINVANTI and for 1 month following administration of CINVANTI or oral aprepitant, whichever is administered last [see Drug Interactions (7.1), Use in Specific Populations (8.3)].

6 ADVERSE REACTIONS

The following clinically significant adverse reactions are described elsewhere in the labeling:

- Hypersensitivity Reactions [see Warnings and Precautions (5.2)]

6.1 Clinical Trials Experience

Because clinical trials are conducted under widely varying conditions, adverse reaction rates observed in the clinical trials of a drug cannot be directly compared to rates in the clinical trials of another drug and may not reflect the rates observed in clinical practice.

The safety of CINVANTI was evaluated as a single-dose in healthy subjects and established from adequate and well-controlled studies of intravenous fosaprepitant and/or oral aprepitant [see Clinical Studies (14)]. Adverse reactions observed in these adequate and well-controlled studies are described below.

Safety of CINVANTI

A total of 200 healthy subjects received a single 130 mg dose of CINVANTI as a 30-minute infusion. Adverse reactions reported in at least 2% of subjects were headache (3%) and fatigue (2%). The safety profile of CINVANTI in 50 healthy subjects who received a single 2-minute injection was similar to that seen with a 30-minute infusion.

Single-Dose Intravenous Fosaprepitant -- HEC

In an active-controlled clinical study in patients receiving HEC, safety was evaluated for 1143 patients receiving a single intravenous dose of fosaprepitant, a prodrug of aprepitant, compared to 1169 patients receiving a 3-day regimen of oral aprepitant [see Clinical Studies (14.1)]. When administered intravenously, fosaprepitant is converted to aprepitant within 30 minutes. The safety profile was generally similar to that seen in prior HEC studies with a 3-day regimen of oral aprepitant. However, infusion-site reactions occurred at a higher incidence in patients in the intravenous fosaprepitant group (3%) compared to those in the oral aprepitant group (0.5%). The reported infusion-site reactions included: infusion-site erythema, infusion-site pruritus, infusion-site pain, infusion-site induration and infusion-site thrombophlebitis.

Adverse reactions associated with oral aprepitant may also be expected to occur with CINVANTI. See the full prescribing information for oral aprepitant for complete safety information.

Single-Dose Intravenous Fosaprepitant -- MEC

In an active-controlled clinical trial in patients receiving MEC, safety was evaluated in 504 patients receiving a single dose of intravenous fosaprepitant in combination with ondansetron and dexamethasone (intravenous fosaprepitant regimen) compared to 497 patients receiving ondansetron and dexamethasone alone (standard therapy). The most common adverse reactions are listed in Table 5.

Table 5. Most Common Adverse Reactions in Patients Receiving MEC [Reported in ≥2% of patients treated with the intravenous fosaprepitant regimen and at a greater incidence than standard therapy.]
 | Intravenous fosaprepitant, ondansetron, and dexamethasone [Intravenous fosaprepitant regimen] (N=504) | Ondansetron and dexamethasone [Standard therapy] (N=497)
Fatigue | 15% | 13%
Diarrhea | 13% | 11%
Neutropenia | 8% | 7%
Asthenia | 4% | 3%
Anemia | 3% | 2%
Peripheral Neuropathy | 3% | 2%
Leukopenia | 2% | 1%
Dyspepsia | 2% | 1%
Urinary Tract Infection | 2% | 1%
Pain In Extremity | 2% | 1%

Infusion-site reactions were reported in 2.2% of patients treated with the intravenous fosaprepitant regimen compared to 0.6% of patients treated with standard therapy. The infusion-site reactions included: infusion-site pain (1.2%, 0.4%), injection-site irritation (0.2%, 0.0%), vessel puncture-site pain (0.2%, 0.0%), and 8 infusion-site thrombophlebitis (0.6%, 0.0%), reported in the intravenous fosaprepitant regimen compared to standard therapy, respectively.

3-Day Oral Aprepitant -- MEC

In 2 active-controlled clinical trials in patients receiving MEC, 868 patients were treated with a 3-day oral aprepitant regimen during Cycle 1 of chemotherapy and 686 of these patients continued into extensions for up to 4 cycles of chemotherapy. In both studies, oral aprepitant was given in combination with ondansetron and dexamethasone (oral aprepitant regimen) and was compared to ondansetron and dexamethasone alone (standard therapy) [see Clinical Studies (14.2)].

In the combined analysis of Cycle 1 data for these 2 studies, adverse reactions were reported in approximately 14% of patients treated with the aprepitant regimen compared with approximately 15% of patients treated with standard therapy. Treatment was discontinued due to adverse reactions in 0.7% of patients treated with the aprepitant regimen compared with 0.2% of patients treated with standard therapy.

The most common adverse reactions reported in patients treated with the oral aprepitant regimen with an incidence of at least 1% and greater than standard therapy are listed in Table 6.

Table 6. Adverse Reactions (≥ 1%) in Patients Receiving MEC with a Greater Incidence in the Oral 3-Day Aprepitant Regimen Relative to Standard Therapy
 | Oral Aprepitant Regimen (N = 868) | Standard Therapy (N = 846)
Fatigue | 1.4 | 0.9
Eructation | 1.0 | 0.1

A listing of adverse reactions reported in less than 1% in patients treated with the oral aprepitant regimen that occurred at an incidence greater than in patients treated with standard therapy are presented in the Less Common Adverse Reactions subsection below.

Less Common Adverse Reactions

Adverse reactions reported in studies in patients treated with the 3-day oral aprepitant regimen with an incidence < 1% and greater than standard therapy are listed in Table 7.

Table 7. Adverse Reactions (incidence < 1%) in Patients Observed in Studies with a Greater Incidence in the Oral Aprepitant Regimen Relative to Standard Therapy
Infection and infestations | candidiasis, staphylococcal infection
Blood and the lymphatic system disorders | anemia, febrile neutropenia
Metabolism and nutrition disorders | weight gain, polydipsia
Psychiatric disorders | disorientation, euphoria, anxiety
Nervous system disorders | dizziness, dream abnormality, cognitive disorder, lethargy, somnolence
Eye disorders | conjunctivitis
Ear and labyrinth disorders | tinnitus
Cardiac disorders | bradycardia, cardiovascular disorder, palpitations
Vascular disorders | hot flush, flushing
Respiratory, thoracic and mediastinal disorders | pharyngitis, sneezing, cough, postnasal drip, throat irritation
Gastrointestinal disorders | nausea, acid reflux, dysgeusia, epigastric discomfort, obstipation, gastroesophageal reflux disease, perforating duodenal ulcer, vomiting, abdominal pain, dry mouth, abdominal distension, feces hard, neutropenic colitis, flatulence, stomatitis
Skin and subcutaneous tissue disorders | rash, acne, photosensitivity, hyperhidrosis, oily skin, pruritus, skin lesion
Musculoskeletal and connective tissue disorders | muscle cramp, myalgia, muscular weakness
Renal and urinary disorders | polyuria, dysuria, pollakiuria
General disorders and administration site condition | edema, chest discomfort, malaise, thirst, chills, gait disturbance
Investigations | alkaline phosphatase increased, hyperglycemia, microscopic hematuria, hyponatremia, weight decreased, neutrophil count decreased

In another chemotherapy-induced nausea and vomiting study, Stevens-Johnson syndrome was reported as a serious adverse reaction in a patient receiving aprepitant with cancer chemotherapy.

The adverse experience profiles in the Multiple-Cycle extensions of HEC and MEC studies for up to 6 cycles of chemotherapy were similar to that observed in Cycle 1.

6.2 Postmarketing Experience

The following adverse reactions have been identified during post-approval use of intravenous fosaprepitant and/or intravenous or oral aprepitant. Because these reactions are reported voluntarily from a population of uncertain size, it is not always possible to reliably estimate their frequency or establish a causal relationship to drug exposure.

Skin and subcutaneous tissue disorders: pruritus, rash, urticaria, Stevens-Johnson syndrome/toxic epidermal necrolysis [see Warnings and Precautions (5.2)].

Immune system disorders: hypersensitivity reactions including anaphylaxis and anaphylactic shock [see Contraindications (4), Warnings and Precautions (5.2)].

Nervous system disorders: ifosfamide-induced neurotoxicity reported after aprepitant and ifosfamide coadministration.

7 DRUG INTERACTIONS

7.1 Effect of Aprepitant on the Pharmacokinetics of Other Drugs

Aprepitant is a substrate, weak-to-moderate (dose-dependent) inhibitor, and an inducer of CYP3A4. Aprepitant is also an inducer of CYP2C9 [see Clinical Pharmacology (12.3)].

Some substrates of CYP3A4 are contraindicated with CINVANTI [see Contraindications (4)]. Dosage adjustment of some CYP3A4 and CYP2C9 substrates may be warranted, as shown in Table 8.

Table 8. Effects of Aprepitant on the Pharmacokinetics of Other Drugs
CYP3A4 Substrates
Pimozide
Clinical Impact | Increased pimozide exposure.
Intervention | CINVANTI is contraindicated [see Contraindications (4)].
Benzodiazepines
Clinical Impact | Increased exposure to midazolam or other benzodiazepines metabolized via CYP3A4 (alprazolam, triazolam) may increase the risk of adverse reactions [see Clinical Pharmacology (12.3)].
Intervention | Monitor for benzodiazepine-related adverse reactions.
Dexamethasone
Clinical Impact | Increased dexamethasone exposure [see Clinical Pharmacology (12.3)].
Intervention | Reduce the dose of oral dexamethasone by approximately 50% [see Dosage and Administration (2.1)].
Methylprednisolone
Clinical Impact | Increased methylprednisolone exposure [see Clinical Pharmacology (12.3)].
Intervention | Reduce the dose of oral methylprednisolone by approximately 50% on Days 1 and 2 for patients receiving HEC and on Day 1 for patients receiving MEC. Reduce the dose of intravenous methylprednisolone by 25% on Days 1 and 2 for patients receiving HEC and on Day 1 for patients receiving MEC.
Chemotherapeutic Agents that are Metabolized by CYP3A4
Clinical Impact | Increased exposure of the chemotherapeutic agent may increase the risk of adverse reactions [see Clinical Pharmacology (12.3)].
Intervention | Vinblastine, vincristine, or ifosfamide or other chemotherapeutic agents; - Monitor for chemotherapeutic-related adverse reactions.; Etoposide, vinorelbine, paclitaxel, and docetaxel; - No dosage adjustment needed.
Hormonal Contraceptives
Clinical Impact | Decreased hormonal exposure during administration of and for 28 days after administration of the last dose of aprepitant [see Warnings and Precautions (5.4), Use in Specific Populations (8.3), and Clinical Pharmacology (12.3)].
Intervention | Effective alternative or back-up methods of contraception (such as condoms or spermicides) should be used during treatment with CINVANTI and for 1 month following administration of CINVANTI or oral aprepitant, whichever is administered last.
Examples | birth control pills, skin patches, implants, and certain IUDs
CYP2C9 Substrates
Warfarin
Clinical Impact | Decreased warfarin exposure and decreased prothrombin time (INR) [see Warnings and Precautions (5.3), Clinical Pharmacology (12.3)].
Intervention | In patients on chronic warfarin therapy, monitor the prothrombin time (INR) in the 2-week period, particularly at 7 to 10 days, following administration of CINVANTI with each chemotherapy cycle.
Other Antiemetic Agents
5-HT3 Antagonists
Clinical Impact | No change in the exposure of the 5-HT3 antagonist [see Clinical Pharmacology (12.3)].
Intervention | No dosage adjustment needed.
Examples | ondansetron, granisetron, dolasetron

7.2 Effect of Other Drugs on the Pharmacokinetics of Aprepitant

Aprepitant is a CYP3A4 substrate [see Clinical Pharmacology (12.3)]. Co-administration of CINVANTI with drugs that are inhibitors or inducers of CYP3A4 may result in increased or decreased plasma concentrations of aprepitant, respectively, as shown in Table 9.

Table 9. Effects of Other Drugs on Pharmacokinetics of Aprepitant
Moderate to Strong CYP3A4 Inhibitors
Clinical Impact | Significantly increased exposure of aprepitant may increase the risk of adverse reactions associated with CINVANTI [see Adverse Reactions (6.1) and Clinical Pharmacology (12.3)].
Intervention | Avoid concomitant use of CINVANTI.
Examples | Moderate inhibitor: diltiazem Strong inhibitors: ketoconazole, itraconazole, nefazodone, troleandomycin, clarithromycin, ritonavir, nelfinavir
Strong CYP3A4 Inducers
Clinical Impact | Substantially decreased exposure of aprepitant in patients chronically taking a strong CYP3A4 inducer may decrease the efficacy of CINVANTI [see Clinical Pharmacology (12.3)].
Intervention | Avoid concomitant use of CINVANTI.
Examples | rifampin, carbamazepine, phenytoin

8 USE IN SPECIFIC POPULATIONS

8.1 Pregnancy

Risk Summary

There are no available data on CINVANTI use in pregnant women to inform a drug-associated risk of adverse developmental outcomes. Avoid use of CINVANTI in pregnant women due to the alcohol content (see Clinical Considerations). In animal reproduction studies, no adverse developmental effects were observed in rats or rabbits exposed during the period of organogenesis to systemic drug concentrations (area under the plasma-concentration time curve [AUC]) of aprepitant approximately equivalent to the exposure at the recommended human dose (RHD) of CINVANTI 130 mg (see Data).

The estimated background risk of major birth defects and miscarriage for the indicated populations is unknown. All pregnancies have a background risk of birth defect, loss, or other adverse outcomes. In the U.S. general population, the estimated background risk of major birth defects and miscarriage in clinically recognized pregnancies is 2 to 4% and 15 to 20%, respectively.

Clinical Considerations

Fetal/Neonatal adverse reactions

CINVANTI contains alcohol. Published studies have demonstrated that alcohol is associated with fetal harm including central nervous system abnormalities, behavioral disorders, and impaired intellectual development. There is no safe level of alcohol exposure in pregnancy; therefore, avoid use of CINVANTI in pregnant women.

Data

Animal Data

In embryofetal development studies in rats and rabbits, aprepitant was administered during the period of organogenesis at oral doses up to 1000 mg/kg twice daily (rats) and up to the maximum tolerated dose of 25 mg/kg/day (rabbits). No embryofetal lethality or malformations were observed at any dose level in either species. The exposures (AUC) in pregnant rats at 1000 mg/kg twice daily and in pregnant rabbits at 125 mg/kg/day were approximately equivalent to the exposure at the RHD of CINVANTI 130 mg. Aprepitant crosses the placenta in rats and rabbits.

8.2 Lactation

Risk Summary

There are no data on the presence of aprepitant in human milk, the effects on the breastfed infant, or the effects on milk production. Aprepitant is present in rat milk. The developmental and health benefits of breastfeeding should be considered along with the mother's clinical need for CINVANTI and any potential adverse effects on the breastfed infant from CINVANTI or from the underlying maternal condition.

8.3 Females and Males of Reproductive Potential

Contraception

Upon administration of CINVANTI, the efficacy of hormonal contraceptives may be reduced. Advise females of reproductive potential using hormonal contraceptives to use an effective alternative or back-up non-hormonal contraceptive (such as condoms or spermicides) during treatment with CINVANTI and for 1 month following the last dose of CINVANTI or oral aprepitant, whichever is administered last [see Warnings and Precautions (5.4), Drug Interactions (7.1), Clinical Pharmacology (12.3)].

8.4 Pediatric Use

The safety and effectiveness of CINVANTI have not been established in pediatric patients.

8.5 Geriatric Use

Of the 1649 adult cancer patients treated with intravenous fosaprepitant in HEC and MEC clinical studies, 27% were aged 65 and over, while 5% were aged 75 and over. Other reported clinical experience with fosaprepitant and/or oral aprepitant has not identified differences in responses between elderly and younger patients. In general, use caution when dosing elderly patients as they have a greater frequency of decreased hepatic, renal or cardiac function and concomitant disease or other drug therapy [see Clinical Pharmacology (12.3)].

8.6 Hepatic Impairment

The pharmacokinetics of aprepitant in patients with mild and moderate hepatic impairment were similar to those of healthy subjects with normal hepatic function. No dosage adjustment is necessary for patients with mild to moderate hepatic impairment (Child-Pugh score 5 to 9). There are no clinical or pharmacokinetic data in patients with severe hepatic impairment (Child-Pugh score greater than 9). Therefore, additional monitoring for adverse reactions in these patients may be warranted when CINVANTI is administered [see Clinical Pharmacology (12.3)].

10 OVERDOSAGE

There is no specific information on the treatment of overdosage with aprepitant.

In the event of overdose, CINVANTI should be discontinued and general supportive treatment and monitoring should be provided. Because of the antiemetic activity of CINVANTI, drug-induced emesis may not be effective in cases of CINVANTI overdosage.

Aprepitant is not removed by hemodialysis.

11 DESCRIPTION

CINVANTI injectable emulsion contains the active ingredient, aprepitant. Aprepitant is a substance P/neurokinin 1 (NK1) receptor antagonist, an antiemetic agent, chemically described as 5-[[(2R,3S)-2-[(1R)-1-[3,5-bis(trifluoromethyl)phenyl]ethoxy]-3-(4-fluorophenyl)-4-morpholinyl]methyl]-1,2-dihydro-3H-1,2,4-triazol-3-one.

Its empirical formula is C23H21F7N4O3, and its structural formula is:

Aprepitant is a white to off-white crystalline solid, with a molecular weight of 534.43. It is practically insoluble in water. Aprepitant is sparingly soluble in ethanol and isopropyl acetate and slightly soluble in acetonitrile.

CINVANTI (aprepitant) injectable emulsion is a sterile, opaque, off-white to amber liquid in a single-dose vial for intravenous use. Each vial contains 130 mg aprepitant in 18 mL of emulsion. The emulsion also contains the following inactive ingredients: egg lecithin (2602 mg), dehydrated alcohol (513 mg), sodium oleate (87 mg), soybean oil (1734 mg), sucrose (973 mg), and water for injection (12142 mg).

12 CLINICAL PHARMACOLOGY

12.1 Mechanism of Action

Aprepitant is a selective high-affinity antagonist of human substance P/neurokinin 1 (NK1) receptors. Aprepitant has little or no affinity for serotonin (5-HT3), dopamine, and corticosteroid receptors. Aprepitant has been shown in animal models to inhibit emesis induced by cytotoxic chemotherapeutic agents, such as cisplatin, via central actions. Animal and human Positron Emission Tomography (PET) studies with aprepitant have shown that it crosses the blood brain barrier and occupies brain NK1 receptors. Animal and human studies show that aprepitant augments the antiemetic activity of the 5-HT3-receptor antagonist ondansetron and the corticosteroid dexamethasone and inhibits both the acute and delayed phases of cisplatin-induced emesis.

12.2 Pharmacodynamics

Cardiac Electrophysiology

In a randomized, double-blind, positive-controlled, thorough QTc study, a single 200 mg intravenous dose of fosaprepitant, a prodrug of aprepitant, had no effect on the QTc interval. In a cross-study comparison, maximum aprepitant concentrations (Cmax) after a single 200 mg dose of fosaprepitant were 1.04- and 1.5-fold higher than that achieved with CINVANTI 130 mg dose and 100 mg dose given as a 30-minute infusion, respectively.

12.3 Pharmacokinetics

Pharmacokinetic parameters following administration of a single intravenous 130 mg dose of CINVANTI administered as a 2-minute injection or 100 mg or 130 mg dose of CINVANTI administered as a 30-minute infusion to healthy subjects are summarized in Table 10.

Table 10. Aprepitant Pharmacokinetic Parameters (Mean (± Standard Deviation)) After Single Dose Intravenous Administration of CINVANTI
 | CINVANTI 130 mg 2-minute intravenous injection | CINVANTI 130 mg 30-minute intravenous infusion | CINVANTI 100 mg 30-minute intravenous infusion
AUC0-72hr (mcg∙hr/mL) | 45.6 (± 15.5) | 43.9 (± 12.7) | 27.8 (± 6.5)
Cmax (mcg/mL) | 13.9 (±3.8) | 6.1 (± 1.5) | 4.3 (± 1.2)

Distribution

Aprepitant is greater than 99% bound to plasma proteins. The mean apparent volume of distribution at steady state (Vdss) was approximately 70 L in humans.

Aprepitant crosses the blood brain barrier in humans [see Clinical Pharmacology (12.1)].

Elimination

Metabolism

Aprepitant undergoes extensive metabolism. In vitro studies using human liver microsomes indicate that aprepitant is metabolized primarily by CYP3A4 with minor metabolism by CYP1A2 and CYP2C19. Metabolism is largely via oxidation at the morpholine ring and its side chains. No metabolism by CYP2D6, CYP2C9, or CYP2E1 was detected.

In healthy young adults, aprepitant accounts for approximately 24% of the radioactivity in plasma over 72 hours following a single oral 300 mg dose of [^14C]-aprepitant, indicating a substantial presence of metabolites in the plasma. Seven metabolites of aprepitant, which are only weakly active, have been identified in human plasma.

Excretion

Aprepitant is eliminated primarily by metabolism; aprepitant is not renally excreted. The apparent terminal half-life ranged from approximately 9 to 13 hours.

Specific Populations

Geriatric Patients

Following oral administration of a single 125 mg dose of aprepitant on Day 1 and 80 mg once daily on Days 2 through 5, the AUC0-24hr of aprepitant was 21% higher on Day 1 and 36% higher on Day 5 in elderly (65 years and older) relative to younger adults. The Cmax was 10% higher on Day 1 and 24% higher on Day 5 in elderly relative to younger adults. These differences are not considered clinically meaningful [see Use in Specific Populations (8.5)].

Male and Female Patients

Following oral administration of a single dose of aprepitant ranging from 40 mg to 375 mg, the AUC0-24hr and Cmax are 9% and 17% higher in females as compared with males. The half-life of aprepitant is 25% lower in females as compared with males and Tmax occurs at approximately the same time. These differences are not considered clinically meaningful.

Racial or Ethnic Groups

Following oral administration of a single dose of aprepitant, ranging from 40 mg to 375 mg, the AUC0-24hr and Cmax are approximately 27% and 19% higher in Hispanics as compared with Caucasians. The AUC0-24hr and Cmax were 74% and 47% higher in Asians as compared to Caucasians. There was no difference in AUC0-24hr or Cmax between Caucasians and Blacks. These differences are not considered clinically meaningful.

Patients with Renal Impairment

A single 240 mg oral dose of aprepitant was administered to patients with severe renal impairment (creatinine clearance less than 30 mL/min/1.73 m^2 as measured by 24-hour urinary creatinine clearance) and to patients with end stage renal disease (ESRD) requiring hemodialysis.

In patients with severe renal impairment, the AUC0-∞ of total aprepitant (unbound and protein bound) decreased by 21% and Cmax decreased by 32%, relative to healthy subjects (creatinine clearance greater than 80 mL/min estimated by Cockcroft-Gault method). In patients with ESRD undergoing hemodialysis, the AUC0-∞ of total aprepitant decreased by 42% and Cmax decreased by 32%. Due to modest decreases in protein binding of aprepitant in patients with renal disease, the AUC of pharmacologically active unbound drug was not significantly affected in patients with renal impairment compared with healthy subjects. Hemodialysis conducted 4 or 48 hours after dosing had no significant effect on the pharmacokinetics of aprepitant; less than 0.2% of the dose was recovered in the dialysate.

Patients with Hepatic Impairment

Following administration of a single 125 mg oral dose of aprepitant on Day 1 and 80 mg once daily on Days 2 and 3 to patients with mild hepatic impairment (Child-Pugh score 5 to 6), the AUC0-24hr of aprepitant was 11% lower on Day 1 and 36% lower on Day 3, as compared with healthy subjects given the same regimen. In patients with moderate hepatic impairment (Child-Pugh score 7 to 9), the AUC0-24hr of aprepitant was 10% higher on Day 1 and 18% higher on Day 3, as compared with healthy subjects given the same regimen. These differences in AUC0-24hr are not considered clinically meaningful. There are no clinical or pharmacokinetic data in patients with severe hepatic impairment (Child-Pugh score greater than 9) [see Use in Specific Populations (8.6)].

Body Mass Index (BMI)

For every 5 kg/m^2 increase in BMI AUC0-24hr and Cmax of aprepitant decrease by 9% and 10%. BMI of subjects in the analysis ranged from 18 kg/m^2 to 36 kg/m^2. This change is not considered clinically meaningful.

Drug Interactions Studies

Aprepitant is a substrate, and a weak-to-moderate (dose-dependent) inhibitor of CYP3A4. Aprepitant is also an inducer of CYP3A4, and CYP2C9. Aprepitant is unlikely to interact with drugs that are substrates for the P-glycoprotein transporter.

Effects of Fosaprepitant/Aprepitant on the Pharmacokinetics of Other Drugs

CYP3A4 Substrates:

Midazolam: Fosaprepitant 150 mg (corresponding to CINVANTI 130 mg) administered as a single intravenous dose on Day 1 increased the AUC0-∞ of midazolam by approximately 1.8-fold on Day 1 and had no effect on Day 4 when midazolam was coadministered as a single oral dose of 2 mg on Days 1 and 4.

Corticosteroids:

Dexamethasone: Fosaprepitant administered as a single 150 mg (corresponding to CINVANTI 130 mg) intravenous dose on Day 1 increased the AUC0-24hr of dexamethasone, administered as a single 8 mg oral dose on Days 1, 2, and Day 3, by approximately 2-fold on Days 1 and 2 [see Dosage and Administration (2.1), Drug Interactions (7.1)].

Methylprednisolone: When oral aprepitant as a 3-day regimen (125 mg/80 mg/80 mg) was administered with intravenous methylprednisolone 125 mg on Day 1 and oral methylprednisolone 40 mg on Days 2 and 3, the AUC of methylprednisolone was increased by 1.34-fold on Day 1 and by 2.5-fold on Day 3 [see Drug Interactions (7.1)].

Chemotherapeutic agents:

Docetaxel: In a pharmacokinetic study, oral aprepitant administered as a 3-day regimen (125 mg/80 mg/80 mg) did not influence the pharmacokinetics of docetaxel [see Drug Interactions (7.1)].

Vinorelbine: In a pharmacokinetic study, oral aprepitant administered as a 3-day regimen (125 mg/80 mg/80 mg) did not influence the pharmacokinetics of vinorelbine to a clinically significant degree [see Drug Interactions (7.1)].

CYP2C9 substrates (Warfarin, Tolbutamide):

Warfarin: A single 125 mg dose of oral aprepitant was administered on Day 1 and 80 mg/day on Days 2 and 3 to subjects who were stabilized on chronic warfarin therapy. Although there was no effect of oral aprepitant on the plasma AUC of R(+) or S(-) warfarin determined on Day 3, there was a 34% decrease in S(-) warfarin trough concentration accompanied by a 14% decrease in the prothrombin time (reported as International Normalized Ratio or INR) 5 days after completion of dosing with oral aprepitant [see Drug Interactions (7.1)].

Tolbutamide: Oral aprepitant, when given as 125 mg on Day 1 and 80 mg/day on Days 2 and 3, decreased the AUC of tolbutamide by 23% on Day 4, 28% on Day 8, and 15% on Day 15, when a single dose of tolbutamide 500 mg was administered prior to the administration of the 3-day regimen of oral aprepitant and on Days 4, 8, and 15. This effect was not considered clinically important.

Other Drugs:

Oral contraceptives: When oral aprepitant was administered as a 3-day regimen (125 mg/80 mg/80 mg) with ondansetron and dexamethasone, and coadministered with an oral contraceptive containing ethinyl estradiol and norethindrone, the trough concentrations of both ethinyl estradiol and norethindrone were reduced by as much as 64% for 3 weeks post-treatment [see Drug Interactions (7.1)].

P-glycoprotein substrates: Aprepitant is unlikely to interact with drugs that are substrates for the P-glycoprotein transporter, as demonstrated by the lack of interaction of oral aprepitant with digoxin in a clinical drug interaction study.

5-HT3 antagonists: In clinical drug interaction studies, aprepitant did not have clinically important effects on the pharmacokinetics of ondansetron, granisetron, or hydrodolasetron (the active metabolite of dolasetron).

Effect of Other Drugs on the Pharmacokinetics of Fosaprepitant/Aprepitant

Rifampin: When a single 375 mg dose of oral aprepitant was administered on Day 9 of a 14-day regimen of 600 mg/day of rifampin, a strong CYP3A4 inducer, the AUC of aprepitant decreased approximately 11-fold and the mean terminal half-life decreased approximately 3-fold [see Drug Interactions (7.2)].

Ketoconazole: When a single 125 mg dose of oral aprepitant was administered on Day 5 of a 10-day regimen of 400 mg/day of ketoconazole, a strong CYP3A4 inhibitor, the AUC of aprepitant increased approximately 5-fold and the mean terminal half-life of aprepitant increased approximately 3-fold [see Drug Interactions (7.2)].

Diltiazem: In a study in 10 patients with mild to moderate hypertension, administration of 100 mg of fosaprepitant as an intravenous infusion with 120 mg of diltiazem, a moderate CYP3A4 inhibitor administered three times daily, resulted in a 1.5-fold increase in the aprepitant AUC and a 1.4-fold increase in the diltiazem AUC.

When fosaprepitant was administered with diltiazem, the mean maximum decrease in diastolic blood pressure was significantly greater than that observed with diltiazem alone [24.3 ± 10.2 mm Hg with fosaprepitant versus 15.6 ± 4.1 mm Hg without fosaprepitant]. The mean maximum decrease in systolic blood pressure was also greater after co-administration of diltiazem with fosaprepitant than administration of diltiazem alone [29.5 ± 7.9 mm Hg with fosaprepitant versus 23.8 ± 4.8 mm Hg without fosaprepitant]. Co-administration of fosaprepitant and diltiazem; however, did not result in any additional clinically significant changes in heart rate or PR interval, beyond those changes observed with diltiazem alone [see Drug Interactions (7.2)].

Paroxetine: Coadministration of once daily doses of oral aprepitant 170 mg, with paroxetine 20 mg once daily, resulted in a decrease in AUC by approximately 25% and Cmax by approximately 20% of both aprepitant and paroxetine. This effect was not considered clinically important.

13 NONCLINICAL TOXICOLOGY

13.1 Carcinogenesis, Mutagenesis, Impairment of Fertility

Carcinogenesis

Carcinogenicity studies were conducted in Sprague-Dawley rats and in CD-1 mice for 2 years. In the rat carcinogenicity studies, animals were treated with oral doses ranging from 0.05 to 1000 mg/kg twice daily. The highest dose produced systemic exposures to aprepitant approximately equivalent to (female rats) or less than (male rats) the human exposure at the CINVANTI RHD of 130 mg. Treatment with aprepitant at doses of 5 to 1000 mg/kg twice daily caused an increase in the incidences of thyroid follicular cell adenomas and carcinomas in male rats. In female rats, it produced hepatocellular adenomas at 5 to1000 mg/kg twice daily and hepatocellular carcinomas and thyroid follicular cell adenomas at 125 to 1000 mg/kg twice daily. In the mouse carcinogenicity studies, the animals were treated with oral doses ranging from 2.5 to 2000 mg/kg/day. The highest dose produced a systemic exposure approximately 2 times the human exposure at the RHD of CINVANTI 130 mg. Treatment with aprepitant produced skin fibrosarcomas at 125 and 500 mg/kg/day doses in male mice.

Mutagenesis

Aprepitant was not genotoxic in the Ames test, the human lymphoblastoid cell (TK6) mutagenesis test, the rat hepatocyte DNA strand break test, the Chinese hamster ovary (CHO) cell chromosome aberration test and the mouse micronucleus test.

Impairment of Fertility

Oral aprepitant did not affect the fertility or general reproductive performance of male or female rats at doses up to the maximum feasible dose of 1000 mg/kg twice daily (providing exposure in male rats lower than the exposure at the RHD of CINVANTI 130 mg and exposure in female rats approximately equivalent to the human exposure).

14 CLINICAL STUDIES

The safety and efficacy of CINVANTI have been established based on adequate and well-controlled adult studies of a single-dose of intravenous fosaprepitant, a prodrug of aprepitant, and a 3-day regimen of oral aprepitant in chemotherapy-induced nausea and vomiting associated with HEC and MEC, respectively. Below is a description of the results of these adequate and well-controlled studies of fosaprepitant/aprepitant in these conditions.

14.1 Prevention of Nausea and Vomiting Associated with HEC

In a randomized, parallel, double-blind, active-controlled study, 150 mg fosaprepitant as a single intravenous infusion (N = 1147) was compared to a 3-day oral aprepitant regimen (N = 1175) in patients receiving a HEC regimen that included cisplatin (≥70 mg/m^2). All patients in both groups received dexamethasone and ondansetron (see Table 11) Patient demographics were similar between the two treatment groups. Of the total 2322 patients, 63% were men, 56% White, 26% Asian, 3% American Indian/Alaska Native, 2% Black, 13% Multi-Racial, and 33% Hispanic/Latino ethnicity. Patient ages ranged from 19 to 86 years of age, with a mean age of 56 years. Other concomitant chemotherapy agents commonly administered were fluorouracil (17%), gemcitabine (16%), paclitaxel (15%), and etoposide (12%).

Table 11. Treatment Regimens in HEC Trial [Fosaprepitant placebo, aprepitant placebo and dexamethasone placebo (in the evenings on Days 3 and 4) were used to maintain blinding.]
 | Day 1 | Day 2 | Day 3 | Day 4
Intravenous Fosaprepitant Regimen
Fosaprepitant | 150 mg intravenously over 20 to 30 minutes approximately 30 minutes prior to chemotherapy | None | None | None
Oral dexamethasone [Dexamethasone was administered 30 minutes prior to chemotherapy treatment on Day 1 and in the morning on Days 2 through 4. Dexamethasone was also administered in the evenings on Days 3 and 4. The 12 mg dose of dexamethasone on Day 1 and the 8 mg once daily dose on Day 2 reflects a dosage adjustment to account for a drug interaction with the fosaprepitant regimen [see Clinical Pharmacology (12.3)].] | 12 mg | 8 mg | 8 mg twice daily | 8 mg twice daily
Ondansetron | Ondansetron [Ondansetron 32 mg intravenous was used in the clinical trial. Although this dose was used in the clinical trial, this is no longer the currently recommended dose. Refer to the ondansetron prescribing information for the current recommended dose.] | None | None | None
Oral Aprepitant Regimen
Aprepitant capsules | 125 mg | 80 mg | 80 mg | None
Oral dexamethasone [Dexamethasone was administered 30 minutes prior to chemotherapy treatment on Day 1 and in the morning on Days 2 through 4. The 12 mg dose of dexamethasone on Day 1 and the 8 mg once daily dose on Days 2 through 4 reflects a dosage adjustment to account for a drug interaction with the oral aprepitant regimen [see Clinical Pharmacology (12.3)].] | 12 mg | 8 mg | 8 mg | 8 mg
Ondansetron | Ondansetron | None | None | None

The efficacy of a single-dose of intravenous fosaprepitant was evaluated based on the primary and secondary endpoints listed in Table 12 and was shown to be non-inferior to that of the 3-day oral aprepitant regimen with regard to complete response in each of the evaluated phases. The pre-specified non-inferiority margin for complete response in the overall phase was 7%. The pre-specified non-inferiority margin for complete response in the delayed phase was 7.3%. The pre-specified non-inferiority margin for no vomiting in the overall phase was 8.2%.

Table 12. Percent of Patients Receiving HEC Responding by Treatment Group and Phase — Cycle 1
ENDPOINTS | Intravenous Fosaprepitant Regimen (N = 1106) [N: Number of patients included in the primary analysis of complete response.] % | Oral aprepitant Regimen (N = 1134) % | Difference [Difference and Confidence interval (CI) were calculated using the method proposed by Miettinen and Nurminen and adjusted for gender.] (95% CI)
PRIMARY ENDPOINT
Complete Response [Complete Response = no vomiting and no use of rescue therapy.]
Overall [Overall = 0 to 120 hours post-initiation of cisplatin chemotherapy.] | 71.9 | 72.3 | -0.4 (-4.1, 3.3)
SECONDARY ENDPOINTS
Complete Response
Delayed phase [Delayed phase = 25 to 120 hours post-initiation of cisplatin chemotherapy.] | 74.3 | 74.2 | 0.1 (-3.5, 3.7)
No Vomiting
Overall | 72.9 | 74.6 | -1.7 (-5.3, 2.0)

14.2 Prevention of Nausea and Vomiting Associated with MEC

Single-Dose Intravenous Fosaprepitant – MEC

In a randomized, parallel, double-blind, active comparator-controlled study, 150 mg fosaprepitant as a single intravenous infusion (N=502) in combination with ondansetron and dexamethasone (intravenous fosaprepitant regimen) was compared with ondansetron and dexamethasone alone (standard therapy) (N=498) (see Table 13) in patients receiving a MEC regimen. Patient demographics were similar between the two treatment groups. Of the total 1,000 patients included in the efficacy analysis, 41% were men, 84% White, 4% Asian, 1% American Indian/Alaska Native, 2% Black, 10% Multi-Racial, and 19% Hispanic/Latino ethnicity. Patient ages ranged from 23 to 88 years of age, with a mean age of 60 years. The most commonly administered MEC chemotherapeutic agents were carboplatin (51%), oxaliplatin (24%), and cyclophosphamide (12%).

Table 13. Treatment Regimens in MEC Trial [Fosaprepitant placebo and dexamethasone placebo (on Day 1) were used to maintain blinding.]
 | Day 1 | Day 2 | Day 3
Intravenous Fosaprepitant Regimen
Fosaprepitant | 150 mg intravenously over 20 to 30 minutes approximately 30 minutes prior to chemotherapy | None | None
Oral Dexamethasone [Dexamethasone was administered 30 minutes prior to chemotherapy treatment on Day 1. The 12 mg dose reflects a dosage adjustment to account for a drug interaction with the fosaprepitant regimen [see Clinical Pharmacology (12.3)].] | 12 mg | None | None
Oral Ondansetron [The first ondansetron dose was administered 30 to 60 minutes prior to chemotherapy treatment on Day 1 and the second dose was administered 8 hours after first ondansetron dose.] | 8 mg for 2 doses | None | None
Standard Therapy
Oral Dexamethasone | 20 mg | None | None
Oral Ondansetron | 8 mg for 2 doses | 8 mg twice daily | 8 mg twice daily

The primary endpoint was complete response (defined as no vomiting and no rescue therapy) in the delayed phase (25 to 120 hours) of chemotherapy-induced nausea and vomiting. The results by treatment group are shown in Table 14.

Table 14. Percent of Patients Receiving MEC Responding by Treatment Group
ENDPOINTS | Intravenous Fosaprepitant Regimen (N = 502) [N: Number of patients included in the intention to treat population.] % | Standard Therapy Regimen (N = 498) % | p-Value | Treatment Difference (95% CI)
PRIMARY ENDPOINT
Complete Response [Complete Response = no vomiting and no use of rescue therapy.]
Delayed phase [Delayed phase = 25 to 120 hours post-initiation of chemotherapy.] | 78.9 | 68.5 | <0.001 | 10.4 (5.1, 15.9)

3-Day Oral Aprepitant -- MEC

In a multicenter, randomized, double-blind, parallel-group, clinical study in breast cancer patients, a 3-day oral aprepitant regimen was compared with a standard of care therapy in patients receiving a MEC regimen that included cyclophosphamide 750 to1500 mg/m^2; or cyclophosphamide 500 to1500 mg/m^2 and doxorubicin (≤ 60 mg/m^2) or epirubicin (≤ 100 mg/m^2). Patients (N = 866) were randomized to either the aprepitant regimen (N = 438) or standard therapy (N = 428). The treatment regimens are defined in Table 15.

In this study, the most common chemotherapy combinations were cyclophosphamide plus doxorubicin (61%); and cyclophosphamide plus epirubicin and fluorouracil (22%).

Of the 438 patients who were randomized to receive the oral aprepitant regimen, 99.5% were women. Of these, approximately 80% were White, 8% Black, 8% Asian, 4% Hispanic, and < 1% Other. The aprepitant-treated patients in this clinical study ranged from 25 to 78 years of age, with a mean age of 53 years; 70 patients were 65 years or older, with 12 patients being over 74 years.

Table 15. Treatment Regimens in MEC Trial [Aprepitant placebo and dexamethasone placebo were used to maintain binding.]
 | Day 1 | Day 2 | Day 3
Oral Aprepitant Regimen
Aprepitant | 125 mg orally [1 hour prior to chemotherapy.] | 80 mg orally | 80 mg orally
Dexamethasone | 12 mg orally [Dexamethasone was administered 30 minutes prior to chemotherapy treatment on Day 1.] | None | None
Ondansetron | 8 mg orally × 2 doses [Ondansetron was administered 30 to 60 minutes prior to chemotherapy treatment on Day 1 and 8 hours after first ondansetron dose.] | None | None
Standard Therapy
Dexamethasone | 20 mg orally | None | None
Ondansetron | 8 mg orally × 2 doses | 8 mg orally twice daily | 8 mg orally twice daily

The antiemetic activity of oral aprepitant was evaluated based on the following endpoints in which emetic episodes included vomiting, retching, or dry heaves:

Primary endpoint:

- complete response (defined as no emetic episodes and no use of rescue therapy as recorded in patient diaries) in the overall phase (0 to 120 hours post-chemotherapy)

Other prespecified endpoints:

- no emesis (defined as no emetic episodes regardless of use of rescue therapy)
- no nausea (maximum nausea visual analogue scale [VAS] score < 5 mm on a 0 to 100 mm scale)
- no significant nausea (maximum VAS score < 25 mm on a 0 to 100 mm scale)
- complete protection (defined as no emetic episodes, no use of rescue therapy, and a maximum VAS score < 25 mm on a 0 to 100 mm scale)
- complete response during the acute and delayed phases.

A summary of the key results from this study is shown in Table 16.

Table 16. Percent of Patients Receiving MEC Responding by Treatment Group and Phase – Cycle 1
ENDPOINTS | Oral Aprepitant Regimen (N = 433) [N: Number of patients included in the primary analysis of complete response.] % | Standard Therapy (N = 424) % | p-Value
PRIMARY ENDPOINT [Overall: 0 to 120 hours post-chemotherapy treatment.]
Complete Response | 51 | 42 | 0.015
OTHER PRESPECIFIED ENDPOINTS
No Emesis | 76 | 59 | NS [NS when adjusted for prespecified multiple comparisons rule; unadjusted p-value < 0.001.]
No Nausea | 33 | 33 | NS
No Significant Nausea | 61 | 56 | NS
No Rescue Therapy | 59 | 56 | NS
Complete Protection | 43 | 37 | NS

In this study, a statistically significantly (p = 0.015) higher proportion of patients receiving the oral aprepitant regimen in Cycle 1 had a complete response (primary endpoint) during the overall phase compared with patients receiving standard therapy. The difference between treatment groups was primarily driven by the "No Emesis Endpoint", a principal component of this composite primary endpoint. In addition, a higher proportion of patients receiving the oral aprepitant regimen in Cycle 1 had a complete response during the acute (0 to 24 hours) and delayed (25 to 120 hours) phases compared with patients receiving standard therapy; however, the treatment group differences failed to reach statistical significance, after multiplicity adjustments.

Additional Patient-Reported Outcomes: In this study, in patients receiving MEC, the impact of nausea and vomiting on patients' daily lives was assessed in Cycle 1 using the FLIE. A higher proportion of patients receiving the oral aprepitant regimen reported minimal or no impact on daily life (64% versus 56%). This difference between treatment groups was primarily driven by the "No Vomiting Domain" of this composite endpoint.

Multiple-Cycle Extension: Patients receiving MEC were permitted to continue into the Multiple-Cycle extension of the study for up to 3 additional cycles of chemotherapy. Antiemetic effect for patients receiving the aprepitant regimen is maintained during all cycles.

Oral Aprepitant Postmarketing Trial: In another multicenter, randomized, double-blind, parallel-group, clinical study in 848 cancer patients, the 3-day oral aprepitant regimen (N = 430) was compared with a standard of care therapy (N = 418) in patients receiving a MEC regimen that included any intravenous dose of oxaliplatin, carboplatin, epirubicin, idarubicin, ifosfamide, irinotecan, daunorubicin, doxorubicin; intravenous cyclophosphamide (less than 1500 mg/m^2); or intravenous cytarabine (greater than 1 g/m^2).

Of the 430 patients who were randomized to receive the oral aprepitant regimen, 76% were women and 24% were men. The distribution by race was 67% White, 6% Black or African American, 11% Asian, and 12% multiracial. Classified by ethnicity, 36% were Hispanic and 64% were non-Hispanic. The aprepitant-treated patients in this clinical study ranged from 22 to 85 years of age, with a mean age of 57 years; approximately 59% of the patients were 55 years or older with 32 patients being over 74 years. Patients receiving the aprepitant regimen were receiving chemotherapy for a variety of tumor types including 50% with breast cancer, 21% with gastrointestinal cancers including colorectal cancer, 13% with lung cancer and 6% with gynecological cancers.

The antiemetic activity of aprepitant was evaluated based on no vomiting (with or without rescue therapy) in the overall period (0 to 120 hours post-chemotherapy) and complete response (defined as no vomiting and no use of rescue therapy) in the overall period.

A summary of the key results from this study is shown in Table 17.

Table 17. Percent of Patients Receiving MEC Responding by Treatment Group for Study 2 – Cycle 1
ENDPOINTS | Oral Aprepitant Regimen (N = 430) [N = Number of patients who received chemotherapy treatment, study drug, and had at least one post-treatment efficacy evaluation.] % | Standard Therapy (N = 418) % | p-Value
No Vomiting Overall | 76 | 62 | < 0.0001
Complete Response Overall | 69 | 56 | 0.0003

In this study, a statistically significantly higher proportion of patients receiving the oral aprepitant regimen (76%) in Cycle 1 had no vomiting during the overall phase compared with patients receiving standard therapy (62%). In addition, a higher proportion of patients receiving the aprepitant regimen (69%) in Cycle 1 had a complete response in the overall phase (0 to 120 hours) compared with patients receiving standard therapy (56%). In the acute phase (0 to 24 hours following initiation of chemotherapy), a higher proportion of patients receiving aprepitant compared to patients receiving standard therapy were observed to have no vomiting (92% and 84%, respectively) and complete response (89% and 80%, respectively). In the delayed phase (25 to 120 hours following initiation of chemotherapy), a higher proportion of patients receiving aprepitant compared to patients receiving standard therapy were observed to have no vomiting (78% and 67%, respectively) and complete response (71% and 61%, respectively).

In a subgroup analysis by tumor type, a numerically higher proportion of patients receiving aprepitant were observed to have no vomiting and complete response compared to patients receiving standard therapy. For gender, the difference in complete response rates between the aprepitant and standard regimen groups was 14% in females (64.5% and 50.3%, respectively) and 4% in males (82.2% and 78.2%, respectively) during the overall phase. A similar difference for gender was observed for the no vomiting endpoint.

16 HOW SUPPLIED/STORAGE AND HANDLING

CINVANTI injectable emulsion is supplied as an opaque, off-white to amber emulsion in a single-dose glass vial containing 130 mg/18 mL (7.2 mg/mL) aprepitant:

NDC 47426-201-01 | 1 single-dose vial per carton

Storage

CINVANTI injectable emulsion vials must be refrigerated, store at 2°C-8°C (36°F-46°F).

CINVANTI injectable emulsion vials can remain at room temperature up to 60 days.

Do not freeze.

17 PATIENT COUNSELING INFORMATION

Advise the patient to read the FDA-approved patient labeling (Patient Information).

Hypersensitivity

Advise patients that hypersensitivity reactions, including anaphylaxis, have been reported [see Warnings and Precautions (5.2)]. Advise patients to stop taking CINVANTI and seek immediate medical attention if they experience signs or symptoms of a hypersensitivity reaction, such as hives, rash and itching, skin peeling or sores, or difficulty in breathing or swallowing, or dizziness, rapid or weak heartbeat or feeling faint.

Drug Interactions

Advise patients to discuss all medications they are taking, including other prescription, non- prescription medication or herbal products [see Contraindications (4), Warnings and Precautions (5.1)].

Warfarin: Instruct patients on chronic warfarin therapy to follow instructions from their healthcare provider regarding blood draws to monitor their INR during the 2-week period, particularly at 7 to 10 days, following initiation of CINVANTI with each chemotherapy cycle [see Warnings and Precautions (5.3)].

Hormonal Contraceptives: Advise patients that administration of CINVANTI may reduce the efficacy of hormonal contraceptives. Instruct patients to use effective alternative or back-up methods of non-hormonal contraception (such as condoms or spermicides) during treatment with CINVANTI and for 1 month following administration of CINVANTI or oral aprepitant, whichever is administered last [see Warnings and Precautions (5.4), Use in Specific Populations (8.3)].

Pregnancy

Advise pregnant women of the potential risk to a fetus and to avoid use of CINVANTI during pregnancy [see Use in Specific Populations (8.1)].

Manufactured for: Heron Therapeutics, Inc., San Diego, CA 92121, USA
Patent: https://herontx.com/patents/
CINVANTI® is a registered trademark of Heron Therapeutics, Inc.
Copyright © 2017-2024 Heron Therapeutics, Inc.
All rights reserved.

PATIENT INFORMATION
CINVANTI® (sin van' tee)
(aprepitant)
injectable emulsion, for intravenous use

What is CINVANTI?
CINVANTI is a prescription medicine used with other medicines that treat nausea and vomiting in adults to prevent nausea and vomiting caused by certain anti-cancer (chemotherapy) medicines.

- CINVANTI is not used to treat nausea and vomiting that you already have.
- It is not known if CINVANTI is safe and effective in children.

Do not receive CINVANTI if you:

- are allergic to aprepitant, or any of the ingredients in CINVANTI. See the end of this leaflet for a complete list of the ingredients in CINVANTI.
- are taking pimozide (ORAP).

Before receiving CINVANTI, tell your healthcare provider about all of your medical conditions, including if you:

- have liver problems.
- are pregnant or plan to become pregnant. CINVANTI may harm your unborn baby.
  - Women who use birth control medicines containing hormones to prevent pregnancy (birth control pills, skin patches, implants, and certain IUDs) should also use a backup method of birth control that does not contain hormones, such as condoms and spermicides, during treatment with CINVANTI and for 1 month after receiving the last dose of CINVANTI.
- are breastfeeding or plan to breastfeed. It is not known if CINVANTI passes into your breast milk. Talk to your healthcare provider about the best way to feed your baby if you receive CINVANTI.

Tell your healthcare provider about all the medicines you take, including prescription and over-the- counter medicines, vitamins, and herbal supplements.
CINVANTI may affect the way other medicines work, and other medicines may affect the way CINVANTI works, causing serious side effects.
Know the medicines you take. Keep a list of them to show your healthcare provider or pharmacist when you get a new medicine.

How will I receive CINVANTI?

- CINVANTI is given on Day 1. It will be given to you by intravenous (IV) injection or infusion in your vein about 30 minutes before you start your chemotherapy treatment.
- If you take the blood thinner medicine warfarin sodium (COUMADIN, JANTOVEN), your healthcare provider may do blood tests after you receive CINVANTI to check your blood clotting.

What are the possible side effects of CINVANTI?
CINVANTI may cause serious side effects, including:

- Serious allergic reactions.Serious allergic reactions can happen during your CINVANTI infusion. Tell your healthcare provider or nurse right away if you get any of these symptoms during or soon after your infusion:
  - trouble breathing or swallowing, shortness of breath or wheezing
  - swelling of your eyes, face, tongue, or throat
  - flushing or redness of your face or skin
  - hives, rash, itching
  - dizziness, a rapid or weak heartbeat, or you feel faint

The most common side effects of CINVANTI include:

- tiredness
- diarrhea
- low white blood cell and red blood cell counts
- weakness
- feeling weak or numb in your arms and legs

- headache
- indigestion
- urinary tract infection
- belching or burping
- pain in your arms and legs

Infusion-site side effects with CINVANTI may include: pain, hardening, redness or itching at the site of infusion. Swelling (inflammation) of a vein caused by a blood clot can also happen at the infusion site. Tell your healthcare provider if you get any infusion-site side effects.
Tell your healthcare provider if you have any side effect that bothers you or that does not go away. These are not all of the possible side effects of CINVANTI. Call your doctor for medical advice about side effects. You may report side effects to FDA at 1-800-FDA-1088.

General information about the safe and effective use of CINVANTI.
Medicines are sometimes prescribed for purposes other than those listed in a Patient Information leaflet. You can ask your healthcare provider or pharmacist for information about CINVANTI that is written for health professionals.

What are the ingredients in CINVANTI?
Active ingredient: aprepitant
Inactive ingredients: egg lecithin, dehydrated alcohol (3.6% alcohol by volume), sodium oleate, soybean oil, sucrose, and water for injection.
Manufactured for: Heron Therapeutics, Inc., San Diego, CA 92121, USA
Patent: https://herontx.com/patents/
CINVANTI® is a registered trademark of Heron Therapeutics, Inc.

Copyright © 2017-2023 Heron Therapeutics, Inc. All rights reserved.
For more information about CINVANTI call 1-844-437-6611 or go to www.CINVANTI.com.

This Patient Information has been approved by the U.S. Food and Drug Administration

Revised: September 2023

PRINCIPAL DISPLAY PANEL - 130 mg/18 mL Vial Carton

NDC 47426-201-01
Rx Only

CINVANTI ®
(aprepitant)
injectable emulsion

130 mg/18 mL
(7.2 mg/mL)

For Intravenous Use Only

Must be refrigerated. Store at
2°C-8°C (36°F-46°F). Do Not Freeze.

1 Sterile Single-Dose Vial
Discard Unused Portion

HERON
THERAPEUTICS

PRINCIPAL DISPLAY PANEL - 130 mg/18 mL Vial Carton - Not For Sale

NDC 47426-201-01
Rx Only

CINVANTI ®
(aprepitant)
injectable emulsion

130 mg/18 mL
(7.2 mg/mL)

For Intravenous Use Only

Must be refrigerated. Store at
2°C-8°C (36°F-46°F). Do Not Freeze.

1 Sterile Single-Dose Vial
Discard Unused Portion

Not For Sale

HERON
THERAPEUTICS